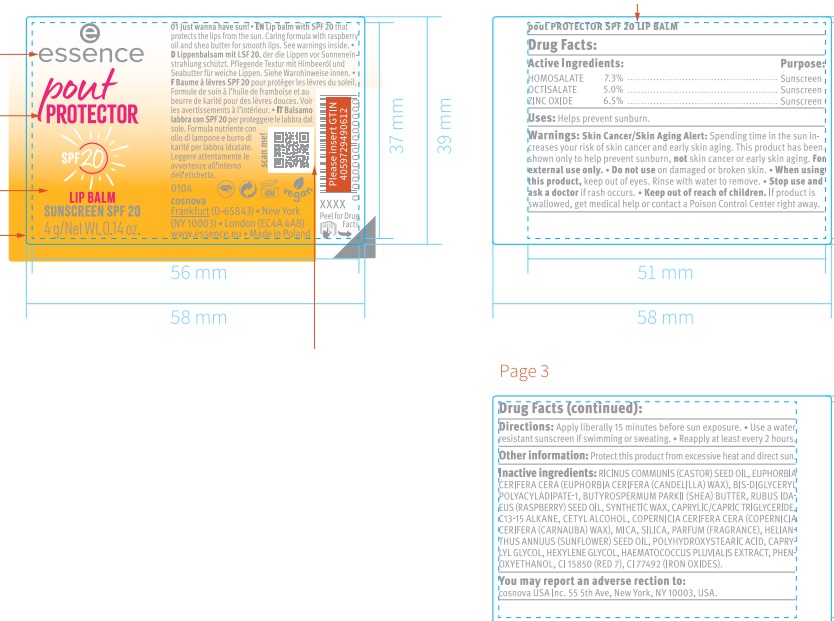 DRUG LABEL: Essence Pout Protector SPF 20 Lip Balm
NDC: 84270-001 | Form: STICK
Manufacturer: cosnova GmbH
Category: otc | Type: HUMAN OTC DRUG LABEL
Date: 20240507

ACTIVE INGREDIENTS: ZINC OXIDE 65 mg/1 g; HOMOSALATE 73 mg/1 g; OCTISALATE 50 mg/1 g
INACTIVE INGREDIENTS: D&C RED NO. 7; FERRIC OXIDE YELLOW; SHEA BUTTER; HAEMATOCOCCUS PLUVIALIS; CETYL ALCOHOL; SILICON DIOXIDE; CAPRYLYL GLYCOL; CANDELILLA WAX; HEXYLENE GLYCOL; RASPBERRY SEED OIL; SYNTHETIC WAX (1200 MW); CASTOR OIL; BIS-DIGLYCERYL POLYACYLADIPATE-1; CARNAUBA WAX; MICA; SUNFLOWER OIL; POLYHYDROXYSTEARIC ACID (2300 MW); PHENOXYETHANOL; MEDIUM-CHAIN TRIGLYCERIDES; C13-15 ALKANE

Essence Pout Protector SPF 20 Lip Balm

Active Ingredients

Homosalate 7.3%

Octisalate 5.0%

Zinc Oxide 6.5%

Purpose

Sunscreen

Uses

- Helps prevent sunburn.

Warnings

Skin Cancer/Skin Aging Alert: Spending time in the sun increases your risk of skin cancer and early skin aging. This product has been shown only to help prevent sunburn, not skin cancer or early skin aging.

For external use only.

Do not use

on damaged or broken skin.

When using this product

keep out of eyes. Rinse with water to remove.

Stop use and ask a doctor

if rash occurs.

Keep out of reach of children.

If product is swallowed, get medical help or contact a Poison Control Center right away.

Directions

- Apply liberally 15 minutes before sun exposure.
- Use a water resistant sunscreen if swimming or sweating.
- Reapply at least every 2 hours.

Other information

Protect this product from excessive heat and direct sun.

Inactive ingredients

RICINUS COMMUNIS (CASTOR) SEED OIL, EUPHORBIA CERIFERA CERA (EUPHORBIA CERIFERA (CANDELILLA) WAX, BIS-DIGLYCERYL POLYACYLADIPATE-1, BUTYROSPERMUM PARKII (SHEA) BUTTER, RUBUS IDAEUS (RASPBERRY) SEED OIL, SYNTHETIC WAX, CAPRYLIC/CAPRIC TRIGLYCERIDE, C13-15 ALKANE, CETYL ALCOHOL, COPERNICIA CERIFERA CERA (COPERNICIA CERIFERA (CARNAUBA) WAX), MICA, SILICA, PARFUM (FRAGRANCE), HELIANTHUS ANNUUS (SUNFLOWER) SEED OIL, POLYHYDROXYSTEARIC ACID, CAPRYLYL GLYCOL, HEXYLENE GLYCOL, HAEMATOCOCCUS PLUVIALIS EXTRACT, PHENOXYETHANOL, CI 15850 (RED 7), CI 77492 (IRON OXIDES).

You may report an adverse reaction to:

cosnova USA Inc 55 5th Ave. New York, NY 10003, USA.